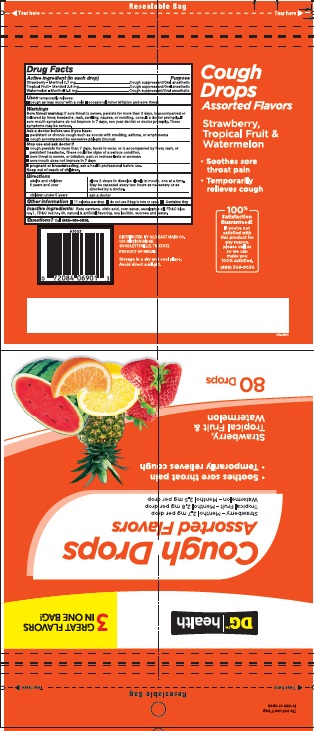 DRUG LABEL: Cough Drops Dollar General Assorted Flavors 80ct
NDC: 75712-042 | Form: LOZENGE
Manufacturer: Dollar General
Category: otc | Type: HUMAN OTC DRUG LABEL
Date: 20251008

ACTIVE INGREDIENTS: MENTHOL 2.8 mg/1 1
INACTIVE INGREDIENTS: SUCROSE; CORN SYRUP; EUCALYPTOL; LECITHIN, SOYBEAN; FD&C RED NO. 40; CITRIC ACID MONOHYDRATE; BETA CAROTENE; FD&C BLUE NO. 1

Active ingredient (in each drop)

Strawberry - Menthol 2.7 mg

Tropical Fruit - Menthol 2.8 mg

Watermelon - Menthol 2.5 mg

Purpose

Cough suppressant / Oral anesthetic

Cough suppressant / Oral anesthetic

Cough suppressant / Oral anesthetic

INDICATIONS AND USAGE

Uses temporarily relieves:

cough as may occur with a cold

occasional minor irritation and sore throat

Warnings

Sore throat warning:if sore throat is severe, persists for more than 2 days, is accompanied or followed by fever, headache, rash, swelling, nausea, or vomiting, consult a doctor promptly. If sore mouth symptoms do not improve in 7 days, see your dentist or doctor promptly. These systems may be serious.

As a doctor before use if you have:

- persistent or chronic cough such as occurs with smoking, asthma, or emphysema
- cough accompanied by excessive phlegm (mucus)

Stop use and consult doctor if

- cough persists for more than 7 days, tends to recur, or is accompanied by fever, rash, or persistent headache. These could be signs of a serious condition.
- sore throat is severe, or irritation, pain or redness lasts or worsens
- sore mouth does not improve in 7 days

PREGNANCY OR BREAST FEEDING

If pregnant of breast-feeding,ask a health professional before use.

Keep out of reach of children.

Directions

adults and children 5 years and over - allow 2 drops to dissolve slowly in mouth, one at a time. May be repeated every 2 hours as necessary or as directed by a doctor.

children under 5 years - ask a doctor

Other information

- 11 calories per drop
- do not use if bag is torn or open
- Contains: Soy

INACTIVE INGREDIENT

Inactive ingredients:Beta carotene, citric acid, corn syrup, eucalyptus oil, FD&C blue no. 1, FD&C red no. 40, glycerin, medium chain triglycerides, natural and artificial flavoring, soy lecithin, sucrose and water.

Questions?Call (888)-309-9030